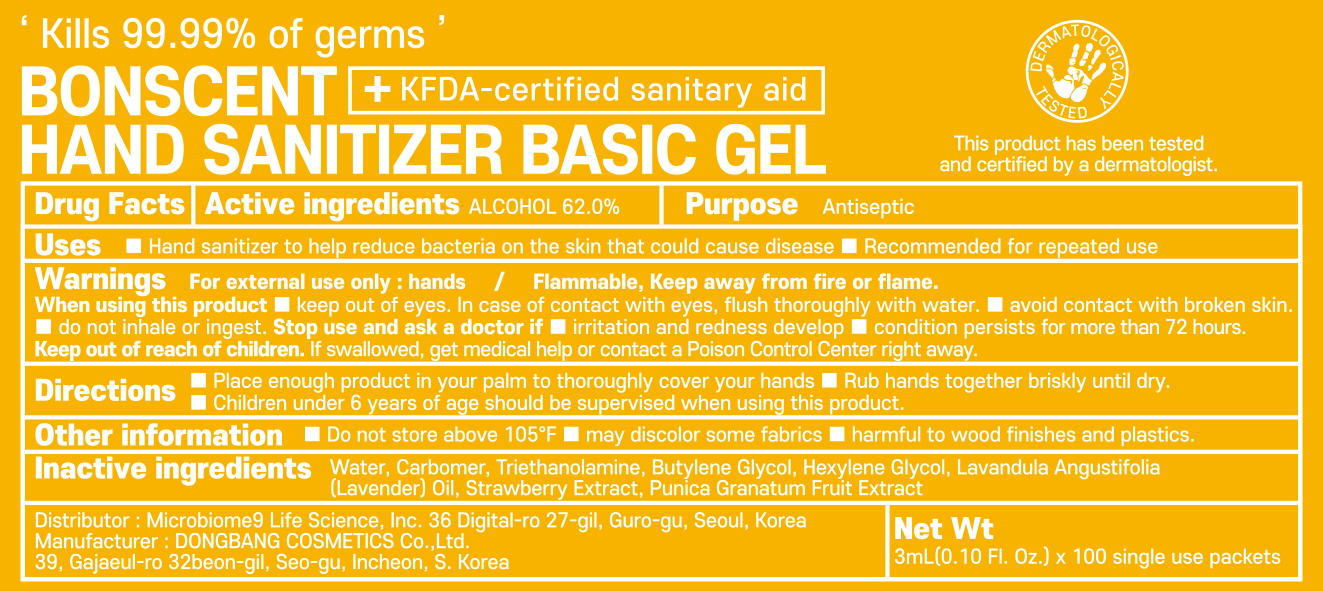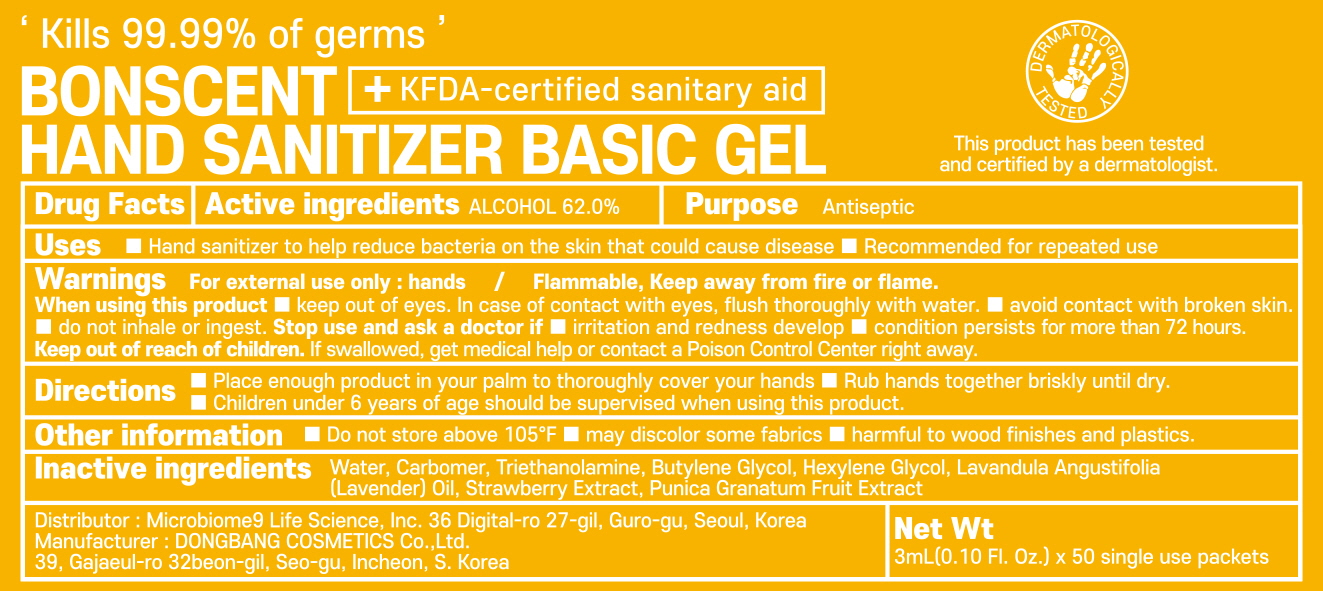 DRUG LABEL: BONSCENT HAND SANITIZER BASIC
NDC: 73981-010 | Form: GEL
Manufacturer: Microbiome9 Life Science
Category: otc | Type: HUMAN OTC DRUG LABEL
Date: 20200327

ACTIVE INGREDIENTS: ALCOHOL 1.86 g/3 mL
INACTIVE INGREDIENTS: Water; CARBOMER HOMOPOLYMER, UNSPECIFIED TYPE; TROLAMINE; Butylene Glycol; Hexylene Glycol

Active Ingredients

Active ingredients: ALCOHOL 62.00%

INACTIVE INGREDIENT

Inactive ingredients:

Water, Carbomer, Triethanolamine, Butylene Glycol, Hexylene Glycol, Lavandula Angustifolia (Lavender) Oil, Strawberry Extract, Punica Granatum Fruit Extract

Purpose

Purpose: Antiseptic

Warnings

For external use only: hands
Flammable, Keep away from fire or flame.
When using this product ■ keep out of eyes. In case of contact with eyes, flush thoroughly with water ■ avoid contact with broken skin. ■ do not inhale or ingest.
Stop use and ask a doctor if ■ irritation and redness develop ■ condition persists for more than 72 hours
Keep out of reach of children. If swallowed, get medical help or contact a Poison Control Center right away.

Keep out of reach of children. If swallowed, get medical help or contact a Poison Control Center right away.

Uses

■ Hand sanitizer to help reduce bacteria on the skin that could cause disease

■ Recommended for repeated use

Directions

■ Place enough product in your palm to thoroughly cover your hands

■ Rub hands together briskly until dry

■ Children under 6 years of age should be supervised when using this product

Other information

■ Do not store above 105°F ■ may discolor some fabrics ■ harmful to wood finishes and plastics